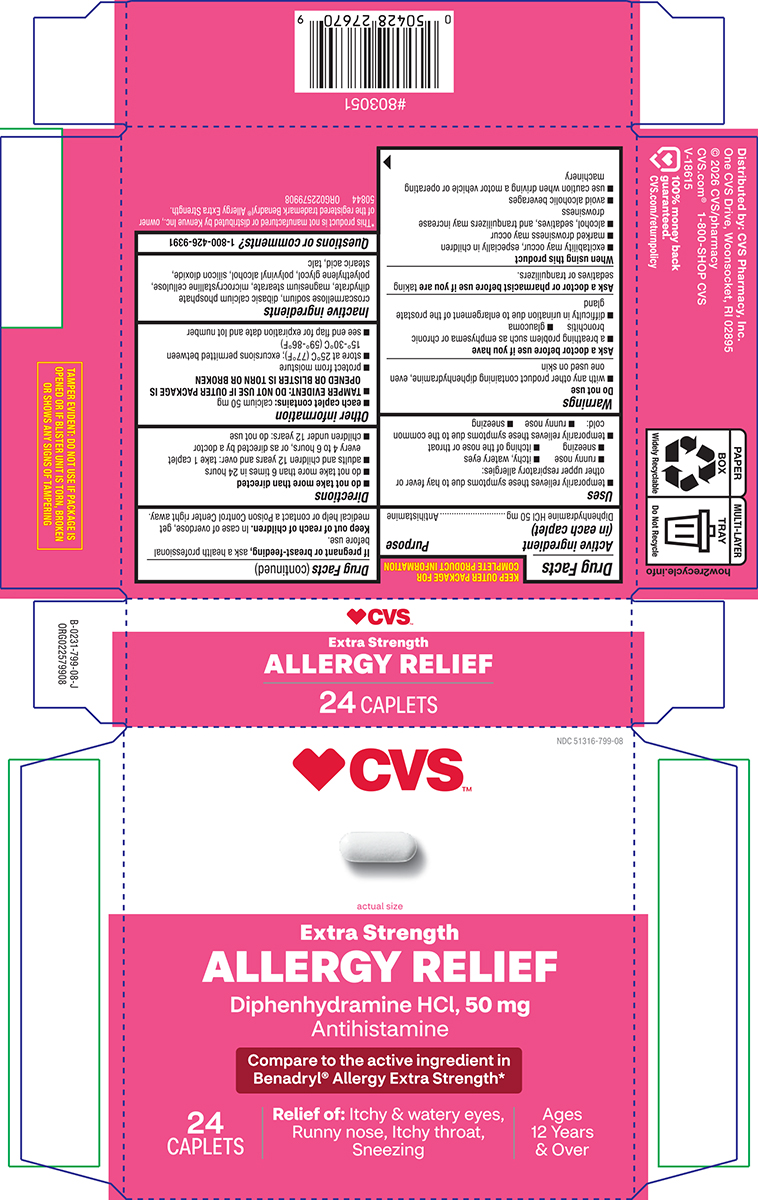 DRUG LABEL: Allergy Relief
NDC: 51316-799 | Form: TABLET, FILM COATED
Manufacturer: CVS WOONSOCKET PRESCRIPTION CENTER, INCORPORATED
Category: otc | Type: HUMAN OTC DRUG LABEL
Date: 20260127

ACTIVE INGREDIENTS: DIPHENHYDRAMINE HYDROCHLORIDE 50 mg/1 1
INACTIVE INGREDIENTS: CROSCARMELLOSE SODIUM; DIBASIC CALCIUM PHOSPHATE DIHYDRATE; MAGNESIUM STEARATE; MICROCRYSTALLINE CELLULOSE; POLYETHYLENE GLYCOL, UNSPECIFIED; POLYVINYL ALCOHOL, UNSPECIFIED; SILICON DIOXIDE; STEARIC ACID; TALC

CVS 44-799

Active ingredient (in each caplet)

Diphenhydramine HCl 50 mg

Purpose

Antihistamine

Uses

- temporarily relieves these symptoms due to hay fever or other upper respiratory allergies:
  - runny nose
  - itchy, watery eyes
  - sneezing
  - itching of the nose or throat
- temporarily relieves these symptoms due to the common cold:
  - runny nose
  - sneezing

Warnings

Do not use

- with any other product containing diphenhydramine, even one used on skin

Ask a doctor before use if you have

- a breathing problem such as emphysema or chronic bronchitis
- glaucoma
- difficulty in urination due to enlargement of the prostate gland

Ask a doctor or pharmacist before use if you are

taking sedatives or tranquilizers.

When using this product

- excitability may occur, especially in children
- marked drowsiness may occur
- alcohol, sedatives, and tranquilizers may increase drowsiness
- avoid alcoholic beverages
- use caution when driving a motor vehicle or operating machinery

If pregnant or breast-feeding,

ask a health professional before use.

Keep out of reach of children.

In case of overdose, get medical help or contact a Poison Control Center right away.

Directions

- do not take more than directed
- do not take more than 6 times in 24 hours
- adults and children 12 years and over: take 1 caplet every 4 to 6 hours, or as directed by a doctor
- children under 12 years: do not use

Other information

- each caplet contains: calcium 50 mg
- TAMPER EVIDENT: DO NOT USE IF OUTER PACKAGE IS OPENED OR BLISTER IS TORN OR BROKEN
- protect from moisture
- store at 25°C (77°F); excursions permitted between 15°-30°C (59°-86°F)
- see end flap for expiration date and lot number

Inactive ingredients

croscarmellose sodium, dibasic calcium phosphate dihydrate, magnesium stearate, microcrystalline cellulose, polyethylene glycol, polyvinyl alcohol, silicon dioxide, stearic acid, talc

Questions or comments?

1-800-426-9391

Principal Display Panel

NDC 51316-799-08

♥ CVS™

actual size

Extra Strength
ALLERGY RELIEF

Diphenhydramine HCl, 50 mg
Antihistamine

Compare to the active ingredient in
Benadryl® Allergy Extra Strength*

24
CAPLETS

Relief of: Itchy & watery eyes,
Runny nose, Itchy throat,
Sneezing

Ages
12 Years
& Over

TAMPER EVIDENT: DO NOT USE IF PACKAGE IS
OPENED OR IF BLISTER UNIT IS TORN, BROKEN
OR SHOWS ANY SIGNS OF TAMPERING

*This product is not manufactured or distributed by Kenvue Inc., owner
of the registered trademark Benadryl® Allergy Extra Strength.
50844 ORG022579908

Distributed by: CVS Pharmacy, Inc.
One CVS Drive, Woonsocket, RI 02895
© 2026 CVS/pharmacy
CVS.com® 1-800-SHOP CVS
V-18615

100% money back
guaranteed.
CVS.com/returnpolicy

CVS 44-799